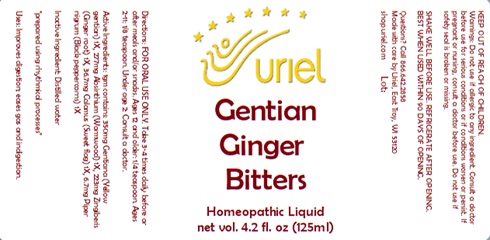 DRUG LABEL: Gentian Ginger Bitters
NDC: 48951-5133 | Form: LIQUID
Manufacturer: Uriel Pharmacy, Inc.
Category: homeopathic | Type: HUMAN OTC DRUG LABEL
Date: 20231215

ACTIVE INGREDIENTS: ACORUS CALAMUS ROOT 1 [hp_X]/1 mL; BLACK PEPPER 1 [hp_X]/1 mL; WORMWOOD 1 [hp_X]/1 mL; GINGER 1 [hp_X]/1 mL; GENTIANA LUTEA ROOT 1 [hp_X]/1 mL
INACTIVE INGREDIENTS: WATER

Gentian Ginger Bitters

INDICATIONS AND USAGE

Directions: FOR ORAL USE ONLY.

DOSAGE AND ADMINISTRATION

Take 3-4 times daily before or after meals and/or snacks. Ages 12 and older: 1/4 teaspoon. Ages 2-11: 1/8 teaspoon. Under age 2: Consult a doctor.

ACTIVE INGREDIENT

Active Ingredients: 1gm contains: 350mg Gentiana (Yellow gentian) 1X, 277mg Absinthium (Wormwood) 1X, 223mg Zingiberis (Ginger root) 1X, 36.7mg Calamus (Sweet flag) 1X, 6.7mg Piper nigrum (Black peppercorns) 1X

Inactive Ingredient: Distilled water

"prepared using rhythmical processes"

PURPOSE

Uses: Improves digestion; eases gas and indigestion.

KEEP OUT OF REACH OF CHILDREN.

WARNINGS

Warnings: Do not use if allergic to any ingredient. Consult a doctor before use for serious conditions or if conditions worsen or persist. If pregnant or nursing, consult a doctor before use. Do not use if safety seal is broken or missing.

Questions? Call 866.642.2858
Made with care by Uriel, East Troy, WI 53120
shopuriel.com Lot: